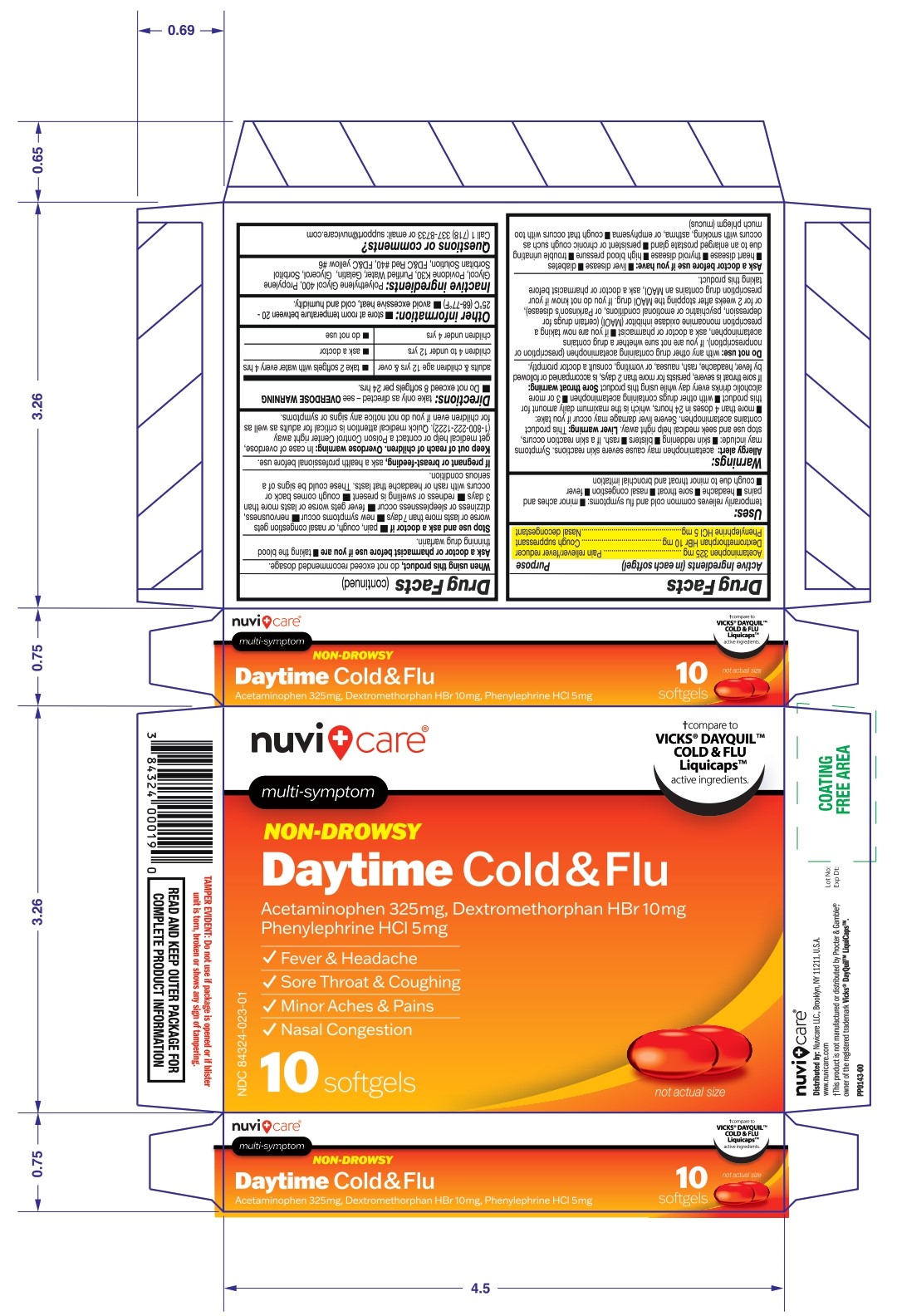 DRUG LABEL: Nuvicare DayTime Cold and Flu Softgel
NDC: 84324-023 | Form: CAPSULE, LIQUID FILLED
Manufacturer: NUVICARE LLC
Category: otc | Type: HUMAN OTC DRUG LABEL
Date: 20250609

ACTIVE INGREDIENTS: ACETAMINOPHEN 325 mg/1 1; DEXTROMETHORPHAN HYDROBROMIDE 10 mg/1 1; PHENYLEPHRINE HYDROCHLORIDE 5 mg/1 1
INACTIVE INGREDIENTS: POLYETHYLENE GLYCOL 400; PROPYLENE GLYCOL; POVIDONE; WATER; Gelatin; Sorbitol; SORBITAN; GLYCERIN; FD&C RED NO. 40; FD&C YELLOW NO. 6

Nuvicare DayTime Cold and Flu Softgel (Acetaminophen 325mg, Dextromethorphan HBr 10mg, Phenylephrine HCl 5mg)

Active ingredients (in each softgel)

Acetaminophen 325mg

Dextromethorphan HBr 10mg

Phenylephrine HCl 5mg

Purpose

Acetaminophen 325mg.....................Pain reliever/fever reducer
Dextromethorphan HBr 10mg..................... Cough suppressant
Phenylephrine HCl 5mg ............................. Nasal decongestant

Uses:

temporarily relieves common cold and flu symptoms:

■ minor aches & pains

■ headache

■ sore throat
■ nasal congestion

■ fever

■ cough due to minor throat & bronchial irritation

Warning

Allergy Alert: acetamenophen may cause severe skin recations. Symptoms may include:

■ skin reddening ■ blisters ■ rash. if a skin reactions occurs, stop use and seek medical help right away.

Liver warning: This product contains acetaminophen. Severe liver damage may occur if you take:
■ more than 4 doses in 24 hrs, which is the maximum daily amount for this product ■ with other drugs containing acetaminophen ■ 3 or more alcoholic drinks daily while using this product.

Sore throat warning: If sore throat is severe, persists for more than 2 days, is accompanied or followed by fever, headache, rash, nausea, or vomiting,consult a doctor promptly.

Do not use:

- with any other drug containing acetaminophen (prescription or nonprescription). If you are not sure whether a drug contains acetaminophen, ask a doctor or pharmacist
- if you are now taking a prescription monoamine oxidase inhibitor (MAOI) (certain drugs for depression, psychiatric or emotional conditions, or Parkinson's disease), or for 2 weeks after stopping the MAOI drug. If you do not know if your prescription drug contains an MAOI, ask a doctor or pharmacist before taking this product.

Ask a doctor before use if you have

■ liver disease

■ diabetes

■ heart disease

■ thyroid disease

■ high blood pressure

■ trouble urinating due to enlarged prostate gland

■ persistent or chronic cough as occurs with smoking, asthma, or emphysema

■ cough that occurs with too much phlegm (mucus)

Ask a doctor or pharmacist before use if you are

- taking the blood thinning drug warfarin

When using this product, do not exceed recommeded dosage.

Stop use and ask a doctor if

- pain, cough or nasal congestion get worse or last more than 7 days
- new symptoms occur
- nervousness, dizziness or sleeplessness occur
- fever gets worse or lasts more than 3 days
- redness or swelling is present
- cough comes back, or occurs with rash or headache that lasts. These could be signs of a serious condition.

PREGNANCY OR BREAST FEEDING

If pregnant or breast-feeding, ask a health professional before use.

Keep out of reach of children.

OVERDOSAGE

Overdose warning: In case of overdose, get medical help or contact a Poison Control Center right away (1-800-222-1222). Quick medical attention is critical for adults as well as for children even if you do not notice any signs or symptoms.

Directions

■ take only as directed- see OVERDOSE WARNING

■ do not exceed 8 softgels per 24 hrs.

Adults and children age 12 yrs and over | take 2 softgels with water every 4 hrs.
Children 4 to under 12 yrs | ask a doctor
Children under 4 yrs | do not use

Other information

■ store at room temperature between 20-25°C (68-77 °F)

■ avoid excessive heat, cold and humidity

Inactive ingredients

Polyethylene Glycol400, Propylene Glycol, Povidone K30, purified water, Gelatin, Glycerol, Sorbitol Sorbitan solution, FD & C Red No. 40, FD &C Yellow No. 6.

Questions or Comments?

Call 1-718-337-8733 or email: support@nuvicare.com